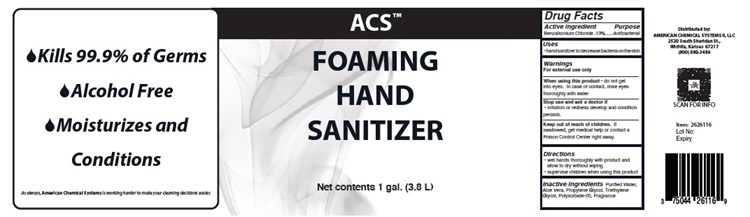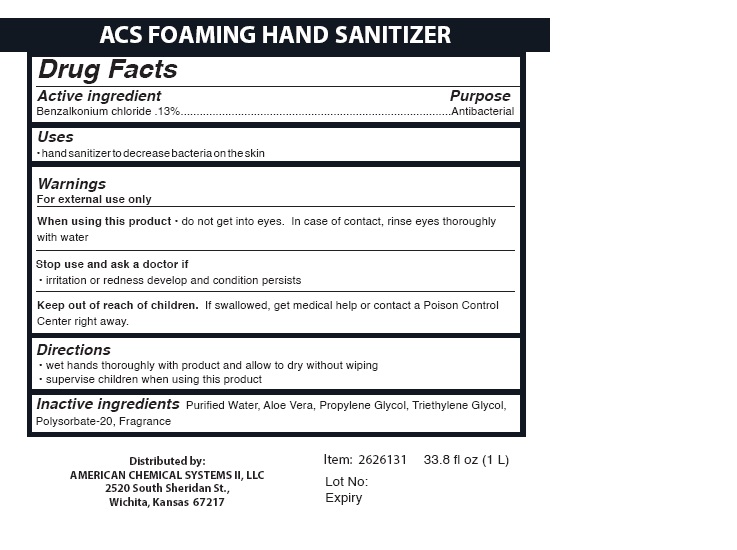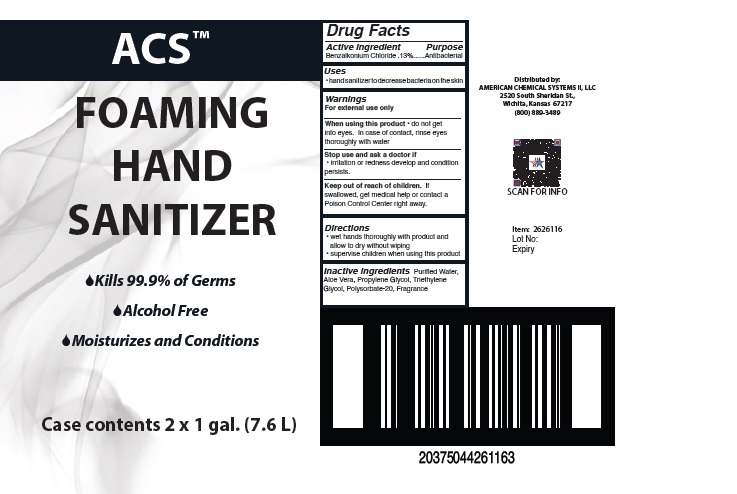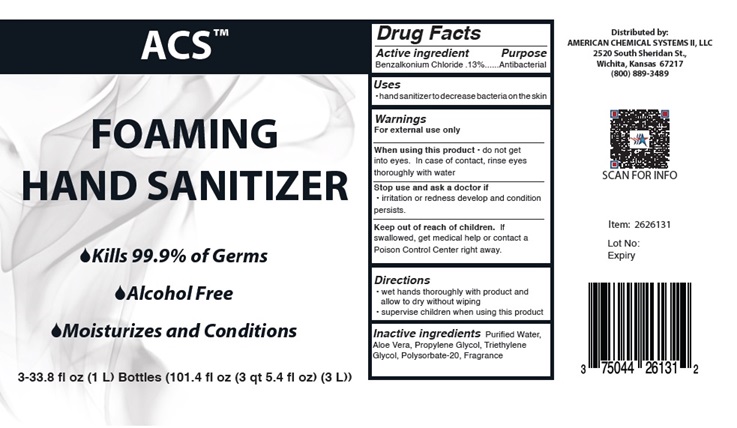 DRUG LABEL: Foaming Hand Sanitizer
NDC: 75044-280 | Form: LIQUID
Manufacturer: American Chemical Systems II, LLC
Category: otc | Type: HUMAN OTC DRUG LABEL
Date: 20251110

ACTIVE INGREDIENTS: BENZALKONIUM CHLORIDE 1.3 g/1000 mL
INACTIVE INGREDIENTS: WATER; ALOE VERA FLOWER; PROPYLENE GLYCOL; TRIETHYLENE GLYCOL; POLYSORBATE 20

ACS™ FOAMING HAND SANITIZER

Drug Facts

Active ingredient
Benzalkonium chloride .13%.......Antibacterial

Purpose
Antibacterial

Uses

• hand sanitizer to decrease bacteria on the skin

Warnings

For external use only

When using this product • do not get
into eyes. In case of contact, rinse eyes thoroughly with water

Stop use and ask a doctor if
• irritation or redness develop and condition
persists.

Keep out of reach of children.

If swallowed, get medical help or contact a Poison Control Center right away.

Directions
• wet hands thoroughly with product and
allow to dry without wiping
• supervise children when using this product

INACTIVE INGREDIENT

Inactive ingredients Purified Water, Aloe Vera, Propylene Glycol, Triethylene Glycol, Polysorbate-20, Fragrance

ACS™ FOAMING HAND SANITIZER Labeling

ACS™

FOAMING
HAND

SANITIZER

Distributed by:
AMERICAN CHEMICAL SYSTEMS II, LLC
2520 South Sheridan St.,
Wichita, Kansas 67217
(800) 889-3489

Lot No:
Expiry

Labeling [2 x 1 gal. (7.6 L)]

Labeling [3-33.8 fl oz (1 L) Bottles (101.4 fl oz (3 qt 5.4 fl oz) (3 L))]

rege